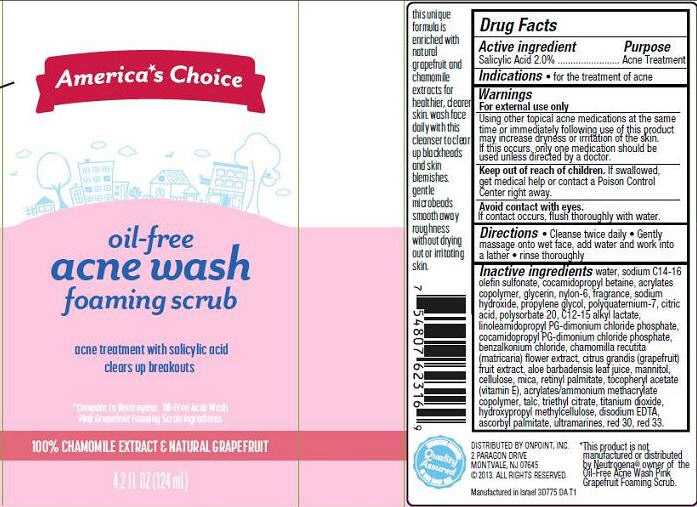 DRUG LABEL: Oil-Free Acne Wash Foaming Scrub
NDC: 42421-775 | Form: GEL
Manufacturer: Emilia Personal Care Inc.
Category: otc | Type: HUMAN OTC DRUG LABEL
Date: 20131112

ACTIVE INGREDIENTS: SALICYLIC ACID 2 g/100 mL
INACTIVE INGREDIENTS: WATER; SODIUM C14-16 OLEFIN SULFONATE; COCAMIDOPROPYL BETAINE; CARBOMER COPOLYMER TYPE A (ALLYL PENTAERYTHRITOL CROSSLINKED); GLYCERIN; SODIUM HYDROXIDE; PROPYLENE GLYCOL; POLYQUATERNIUM-7 (70/30 ACRYLAMIDE/DADMAC; 1600000 MW); CITRIC ACID MONOHYDRATE; POLYSORBATE 20; C12-15 ALKYL LACTATE; LINOLEAMIDOPROPYL PG-DIMONIUM CHLORIDE PHOSPHATE; COCAMIDOPROPYL PG-DIMONIUM CHLORIDE PHOSPHATE; BENZALKONIUM CHLORIDE; CHAMOMILE; PUMMELO; ALOE VERA LEAF; MANNITOL; CELLULOSE, MICROCRYSTALLINE; MICA; VITAMIN A PALMITATE; .ALPHA.-TOCOPHEROL ACETATE; AMMONIO METHACRYLATE COPOLYMER TYPE A; TALC; TRIETHYL CITRATE; TITANIUM DIOXIDE; HYPROMELLOSE 2910 (6 MPA.S); EDETATE DISODIUM; ASCORBYL PALMITATE; ULTRAMARINE BLUE; D&C RED NO. 30; D&C RED NO. 33

America*s Choice Oil-Free Acne Wash

Active ingredient

Salicylic Acid 2.0%

Purpose

Acne Treatment

Indications

- for the treatment of acne

Warnings

For external use only.

Using other topical acne medications at the same time or immediately following use of this product may increase dryness or irritation of the skin. If this occurs, only one medication should be used unless directed by a doctor.

Keep Out of Reach of Children.

If swallowed, get medical help or contact a Poison Control Center right away.

Avoid contact with eyes.

If contact occurs, flush thoroughly with water.

Directions

- Clean twice daily
- Gently massage onto wet face, add water and work into a lather
- Rinse thoroughly

Inactive ingredients

water, sodium C14-16 olefin sulfonate, cocamidopropyl betaine, acrylates copolymer, glycerin, nylon-6, fragrance, sodium hydroxide, propylene glycol, polyquaternium-7, citric acid, polysorbate 20, C12-15 alkyl lactate, linoleamidopropyl PG-dimonium chloride phosphate, propylene glycol, cocamidopropyl PG-dimonium chloride phosphate, benzalkonium chloride, chamomilla recutita (matricaria) flower extract, citrus grandis (grapefruit) fruit extract, aloe barbadensis leaf juice, mannitol, cellulose, mica, retinyl palmitate, tocopheryl acetate (vitamin E), acrylates/ammonium methacrylate copolymer, talc, triethyl citrate, titanium dioxide, hydroxypropyl methylcellulose, disodium EDTA, ascorbyl palmitate, ultramarines, red 30, red 33

Package/Label Principal Display Panel

America*s Choice
oil-free acne wash
foaming scrub

acne treatment with salicylic acid

clears up breakouts

*Compare to Neutrogena Oil-Free Acne Wash
Pink Grapefruit Foaming Scrub ingredients

100% Chamomile Extract & Natural Grapefruit

4.2 Fl Oz (124 mL)

Distributed by Onpoint, Inc.
2 Paragon Drive
Montvale, NJ 07645
©2013 All Rights Reserved.

Manufactured in Israel 3D775 0A T1

*This product is not manufactured or distributed by Neutrogena® owner of the Oil-Free Acne Wash Pink Grapefruit Foaming Scrub.

Label